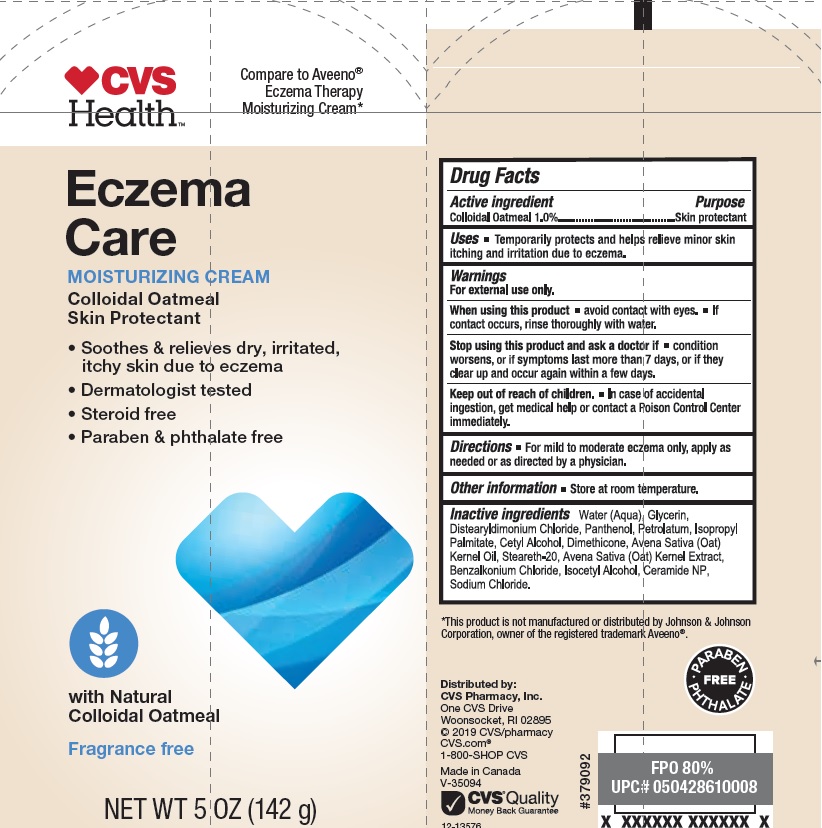 DRUG LABEL: Eczema Care
NDC: 59779-355 | Form: LOTION
Manufacturer: CVS Pharmacy
Category: otc | Type: HUMAN OTC DRUG LABEL
Date: 20190201

ACTIVE INGREDIENTS: OATMEAL 10 mg/1 mL
INACTIVE INGREDIENTS: WATER; GLYCERIN; DISTEARYLDIMONIUM CHLORIDE; PANTHENOL; PETROLATUM; ISOPROPYL PALMITATE; CETYL ALCOHOL; DIMETHICONE; OAT KERNEL OIL; STEARETH-20; BENZALKONIUM CHLORIDE; ISOCETYL ALCOHOL; CERAMIDE NP; SODIUM CHLORIDE

Drug Facts

Active ingredient

Colloidal Oatmeal 1%

Purpose

Skin protectant

Uses

- Temporarily protects and helps relieve minor skin itching and irritation due to eczema.

Warnings

For external use only

When using this product

- avoid contact with eyes.
- if contact occurs, rinse thoroughly with water.

Stop using this product and ask a doctor if

- condition worsens, or if symptoms last more than 7 days, or if they clear up and occur again within a few days.

Keep out of reach of children.

- In case of accidental ingestion, get medical help or contact a Poison Control Center immediately.

Directions

- For mild to moderate eczema only, apply as needed or as directed by a physician.

Other information

- Store at room temperature.

Inactive ingredients

Water (Aqua), Glycerin, Distearyldimonium Chloride, Panthenol, Petrolatum, Isopropyl Palmitate, Cetyl Alcohol, Dimethicone, Avena Sativa (Oat) Kernel Oil, Steareth-20, Avena Sativa (Oat) Kernel Extract, Benzalkonium Chloride, Isocetyl Alcohol, Ceramide NP, Sodium Chloride.